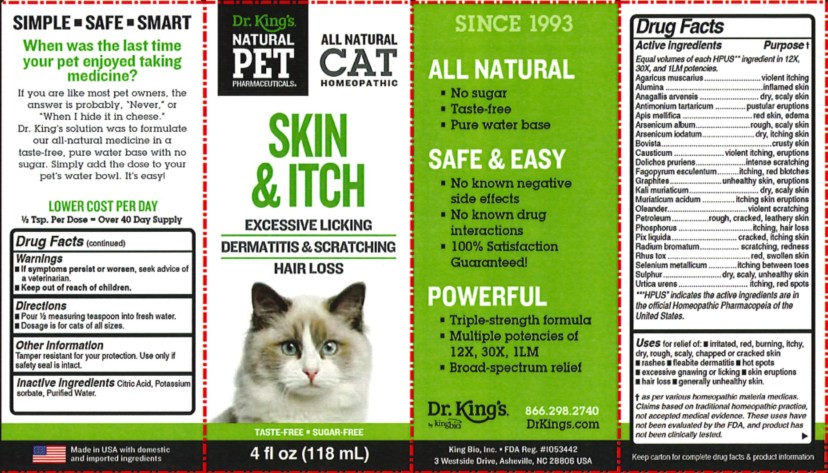 DRUG LABEL: Skin and Itch
NDC: 57955-4701 | Form: LIQUID
Manufacturer: King Bio Inc.
Category: homeopathic | Type: OTC ANIMAL DRUG LABEL
Date: 20250506

ACTIVE INGREDIENTS: AMANITA MUSCARIA FRUITING BODY 12 [hp_X]/118 mL; ALUMINUM OXIDE 12 [hp_X]/118 mL; LYSIMACHIA ARVENSIS WHOLE 12 [hp_X]/118 mL; ANTIMONY POTASSIUM TARTRATE 12 [hp_X]/118 mL; APIS MELLIFERA 12 [hp_X]/118 mL; ARSENIC TRIOXIDE 12 [hp_X]/118 mL; ARSENIC TRIIODIDE 12 [hp_X]/118 mL; LYCOPERDON UTRIFORME FRUITING BODY 12 [hp_X]/118 mL; CAUSTICUM 12 [hp_X]/118 mL; MUCUNA PRURIENS FRUIT TRICHOME 12 [hp_X]/118 mL; FAGOPYRUM ESCULENTUM WHOLE 12 [hp_X]/118 mL; GRAPHITE 12 [hp_X]/118 mL; POTASSIUM CHLORIDE 12 [hp_X]/118 mL; HYDROCHLORIC ACID 12 [hp_X]/118 mL; NERIUM OLEANDER LEAF 12 [hp_X]/118 mL; KEROSENE 12 [hp_X]/118 mL; PHOSPHORUS 12 [hp_X]/118 mL; PINE TAR 12 [hp_X]/118 mL; RADIUM BROMIDE 12 [hp_X]/118 mL; TOXICODENDRON PUBESCENS LEAF 12 [hp_X]/118 mL; SELENIUM 12 [hp_X]/118 mL; SULFUR 12 [hp_X]/118 mL; URTICA URENS WHOLE 12 [hp_X]/118 mL
INACTIVE INGREDIENTS: ANHYDROUS CITRIC ACID; POTASSIUM SORBATE; WATER

Skin and Itch

Warnings

If symptoms persist or worsen, seek advice of
a veterinarian.

Keep out of reach of children.

Reference image:Skin and Itch.jpg

Directions

Pour ½ measuring teaspoon into fresh water.

Dosage is for cats of all sizes.

Reference image:Skin and Itch.jpg

Other information

Tamper resistant for your protection.

Use only if safety seal is intact.

This product has not been clinically tested.

Questions? Call 866.298.2740

King Bio, Inc. 3 Westside Drive

Asheville, NC 2806 USA

FDA Reg. #1053442

For latest product information and instructions: www.DrKings.com

Reference image:Skin and Itch.jpg

Keep out of reach of children.

Reference image:Skin and Itch.jpg

Ingredients

Equal volumes of each HPUS** ingredient in 12X,
30X, and 1LM potencies.

Agaricus muscarius, Alumina, Anagallis arvensis, Antimonium tartaricum, Apis mellifica, Arsenicum album, Arsenicum iodatum, Bovista, Causticum, Dolichos pruriens, Fagopyrum esculentum, Graphites, Kali muriaticum, Muriaticum acidum, Oleander, Petroleum, Phosphorus, Pix liquida, Radium bromatum, Rhus tox, Selenium metallicum, Sulphur, Urtica urens.

**“HPUS” indicates the active ingredients are in the official Homeopathic Pharmacopeia of the United States.

Reference image:Skin and Itch.jpg

Uses

For relief of:

Irritated, red, burning, itchy, dry, rough, scaly, chapped or cracked skin

Rashes

Fleabite dermatitis

Hot spots

Excessive gnawing or licking

Skin eruptions

Hair loss

Generally unhealthy skin

† as per various homeopathic materia medicas.
Claims based on traditional homeopathic practice,
not accepted medical evidence. These uses have
not been evaluated by the FDA, and product has
not been clinically tested

Reference image:Skin and Itch.jpg

Inactive ingredients

Citric Acid, Potassium sorbate, and Purified Water.

Reference image:Skin and Itch.jpg

Active ingredients Purpose †
Equal volumes of each HPUS** ingredient in 12X,
30X, and 1LM potencies.

Agaricus muscarius ...........................violent itching
Alumina ...........................................inflamed skin
Anagallis arvensis ............................dry, scaly skin
Antimonium tartaricum ................pustular eruptions
Apis mellifica ................................red skin, edema
Arsenicum album...........................rough, scaly skin
Arsenicum iodatum........................ dry, itching skin
Bovista.................................................crusty skin
Causticum ........................violent itching, eruptions
Dolichos pruriens..........................intense scratching
Fagopyrum esculentum..............itching, red blotches
Graphites..........................unhealthy skin, eruptions
Kali muriaticum..................................dry, scaly skin
Muriaticum acidum .................itching skin eruptions
Oleander......................................violent scratching
Petroleum ...................rough, cracked, leathery skin
Phosphorus ...................................itching, hair loss
Pix liquida ...............................cracked, itching skin
Radium bromatum......................scratching, redness
Rhus tox ...................................... red, swollen skin
Selenium metallicum .................itching between toes
Sulphur...............................dry, scaly, unhealthy skin
Urtica urens ....................................itching, red spot

**“HPUS” indicates the active ingredients are in
the official Homeopathic Pharmacopeia of the
United States.

Reference image:Skin and Itch.jpg